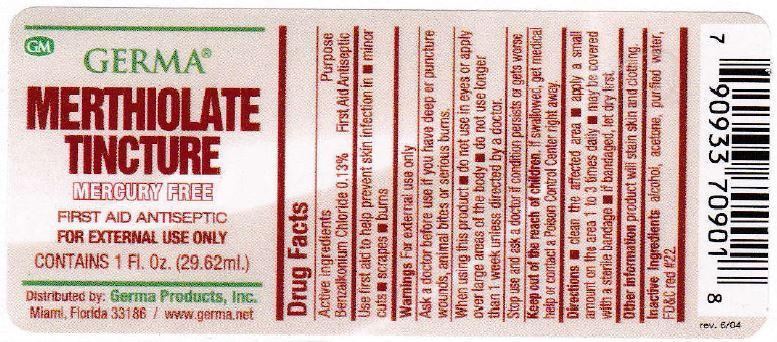 DRUG LABEL: Merthiolate
NDC: 10095-005 | Form: CREAM
Manufacturer: World Perfumes, Inc
Category: otc | Type: HUMAN OTC DRUG LABEL
Date: 20150505

ACTIVE INGREDIENTS: BENZALKONIUM CHLORIDE 0.13 g/100 g
INACTIVE INGREDIENTS: ALCOHOL; ACETONE; WATER; D&C RED NO. 22

Active Ingredients Purpose

Benzalkonium Chloride 0.13% First Aid Antiseptic

PURPOSE

Use first aid to help prevent skin infection in

- minor cuts
- scrapes
- burns

KEEP OUT OF REACH OF CHILDREN

Keep out of the reach of children. If swallowed, get medical help or contact a Poison Control Center right away.

INDICATIONS AND USAGE

Merthiolate Tincture

Mercury Free

First Aid Antiseptic

For External Use Only

Directions

- clean the affected area
- apply a small amount on the area 1 to 3 times daily
- may be covered by a sterile bandage
- if bandaged, let dry first

Warnings

- For external use only
- Ask a doctor before use if you have deep or puncture wounds, animal bites or serious burns.
- When using this product
- do not use in eyes or apply over large areas of the body
- do not use longer than 1 week unless directed by a doctor
- Stop use and ask a doctor if condition persists or gets worse

INACTIVE INGREDIENT

Inactive Ingredients alcohol, acetone, purified water, FD&C red #22